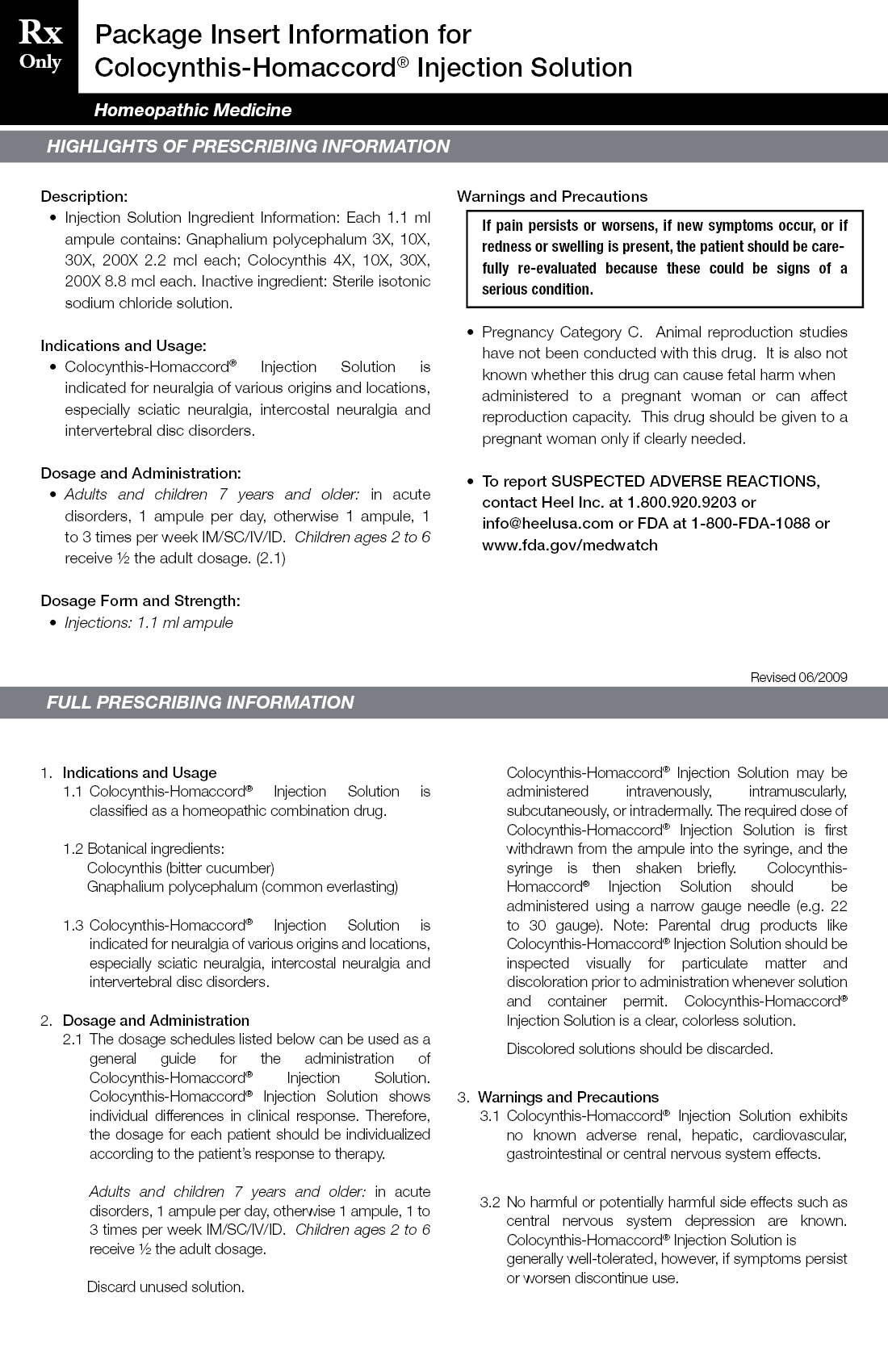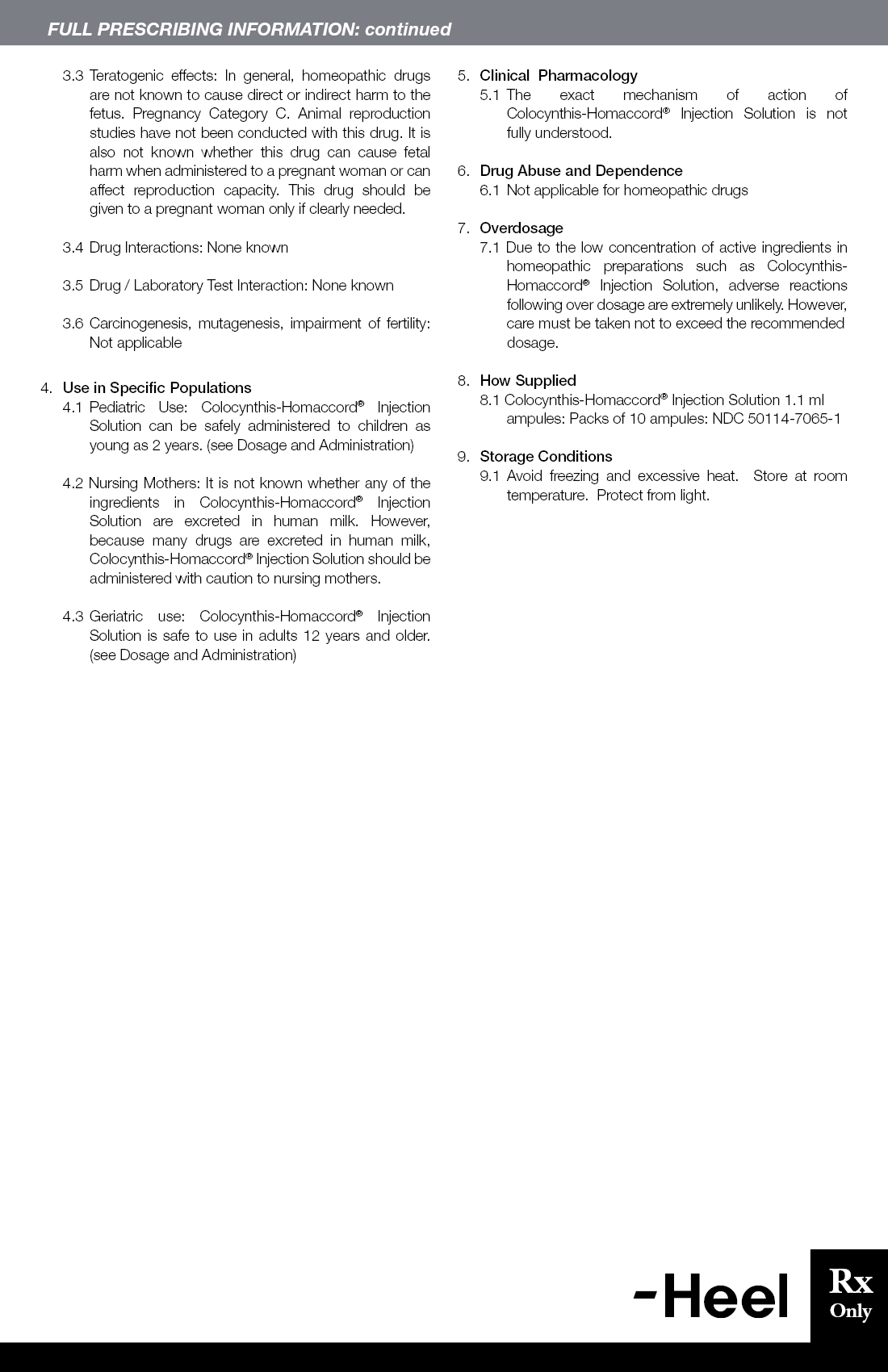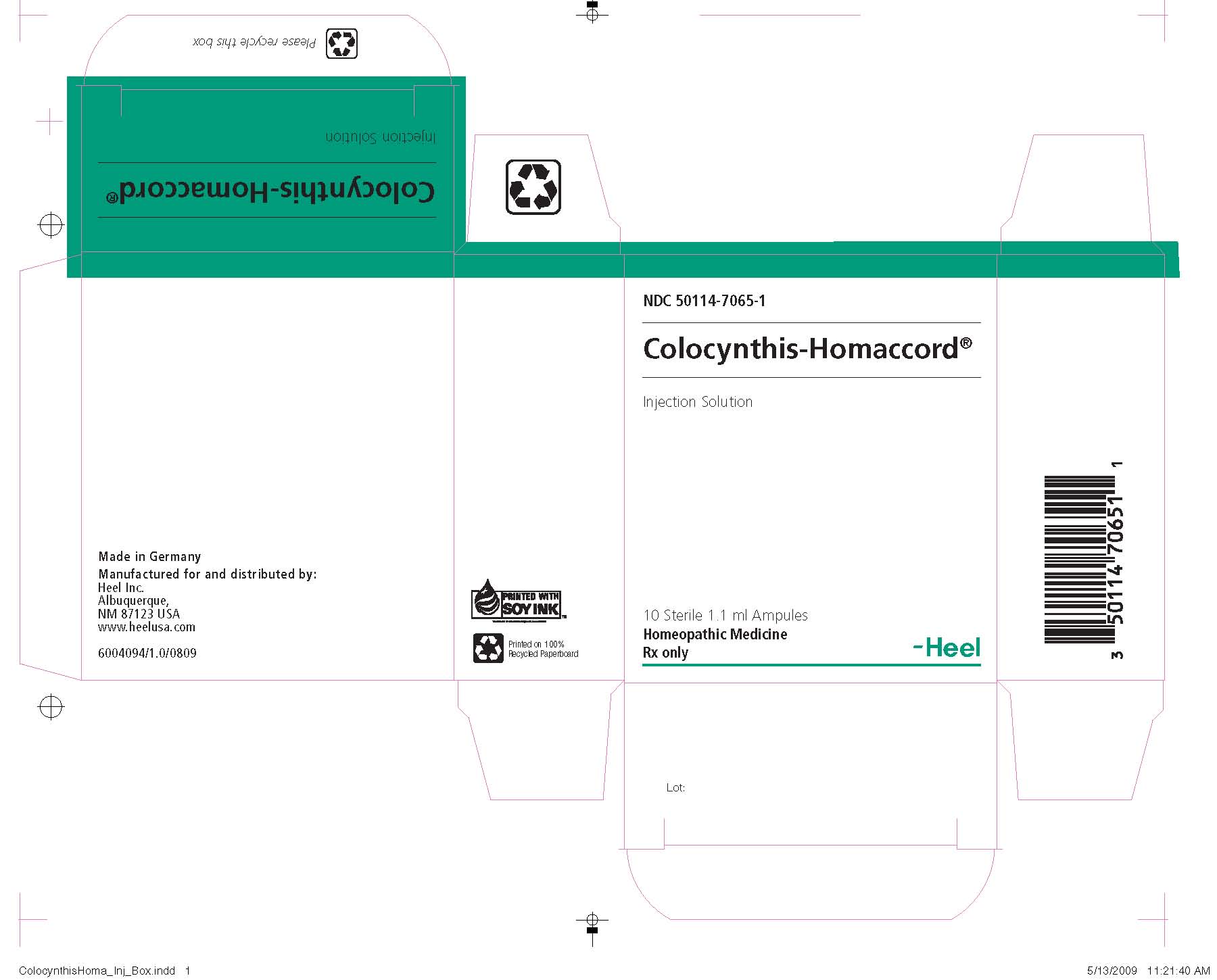 DRUG LABEL: Colocynthis Homaccord
								
NDC: 68275-320 | Form: INJECTION
Manufacturer: JENAHEXAL PHARMA GMBH 
Category: homeopathic | Type: HUMAN PRESCRIPTION DRUG LABEL
Date: 20090909

ACTIVE INGREDIENTS: GNAPHALIUM 3 [hp_X]/1.1 mL; GNAPHALIUM 10 [hp_X]/1.1 mL; GNAPHALIUM 30 [hp_X]/1.1 mL; GNAPHALIUM 200 [hp_X]/1.1 mL; CITRULLUS COLOCYNTHIS FRUIT WITHOUT SEED 4 [hp_X]/1.1 mL; CITRULLUS COLOCYNTHIS FRUIT WITHOUT SEED 10 [hp_X]/1.1 mL; CITRULLUS COLOCYNTHIS FRUIT WITHOUT SEED 30 [hp_X]/1.1 mL; CITRULLUS COLOCYNTHIS FRUIT WITHOUT SEED 200 [hp_X]/1.1 mL

Colocynthis Homaccord

Description:
• Injection Solution Ingredient Information: Each 1.1ml ampule contains: Gnaphalium polycephalum 3X,10X,30X,200X 2.2mcl each; Colocynthis 4X,10X,30X,200X 8.8mcl each. Inactive ingredient: Sterile isotonic sodium chloride solution.

Indications and Usage:
• Colocynthis-Homaccord® Injection Solution is indicated for neuralgia of various origins and locations, especially sciatic neuralgia, intercostal neuralgia and intervertebral disc disorders.

Dosage and Administration:
• Adults and children 7 years and older: in acute disorders, 1 ampule per day, otherwise 1 ampule, 1 to 3 times per week IM/SC/IV/ID. Children ages 2 to 6 receive ½ the adult dosage. (2.1)

Dosage Form and Strength:
• Injections: 1.1ml ampule

Warnings and Precautions
If pain persists or worsens, if new symptoms occur, or if redness or swelling is present, the patient should be carefully re-evaluated because these could be signs of a serious condition.
• Pregnancy Category C. Animal reproduction studies have not been conducted with this drug. It is also not known whether this drug can cause fetal harm when administered to a pregnant woman or can affect reproduction capacity. This drug should be given to a pregnant woman only if clearly needed.
• To report SUSPECTED ADVERSE REACTIONS, contact Heel Inc. at 1.800.920.9203 or info@heelusa.com or FDA at 1-800-FDA-1088 or www.fda.gov/medwatch

1. Indications and Usage
1.1 Colocynthis-Homaccord® Injection Solution is classifed as a homeopathic combination drug.
1.2 Botanical ingredients: Colocynthis (bitter cucumber) Gnaphalium polycephalum (common everlasting)
1.3 Colocynthis-Homaccord® Injection Solution is indicated for neuralgia of various origins and locations, especially sciatic neuralgia, intercostal neuralgia and intervertebral disc disorders.

2. Dosage and Administration
2.1 The dosage schedules listed below can be used as a general guide for the administration of Colocynthis-Homaccord® Injection Solution. Colocynthis-Homaccord® Injection Solution shows individual differences in clinical response. Therefore, the dosage for each patient should be individualized according to the patient’s response to therapy.
Adults and children 7 years and older: in acute disorders, 1 ampule per day, otherwise 1 ampule, 1 to 3 times per week IM/SC/IV/ID. Children ages 2 to 6 receive ½ the adult dosage.
Discard unused solution.

Colocynthis-Homaccord® Injection Solution may be administered intravenously, intramuscularly, subcutaneously, or intradermally. The required dose of Colocynthis-Homaccord® Injection Solution is first withdrawn from the ampule into the syringe, and the syringe is then shaken briefy. Colocynthis-Homaccord® Injection Solution should be administered using a narrow gauge needle (e.g. 22 to 30 gauge). Note: Parental drug products like Colocynthis-Homaccord® Injection Solution should be inspected visually for particulate matter and discoloration prior to administration whenever solution and container permit. Colocynthis-Homaccord® Injection Solution is a clear, colorless solution. Discolored solutions should be discarded.

3. Warnings and Precautions
3.1 Colocynthis-Homaccord® Injection Solution exhibits no known adverse renal, hepatic, cardiovascular, gastrointestinal or central nervous system effects.
3.2 No harmful or potentially harmful side effects such as central nervous system depression are known. Colocynthis-Homaccord® Injection Solution is generally well-tolerated, however, if symptoms persist or worsen discontinue use.
3.3 Teratogenic effects: In general, homeopathic drugs are not known to cause direct or indirect harm to the fetus. Pregnancy Category C. Animal reproduction studies have not been conducted with this drug. It is also not known whether this drug can cause fetal harm when administered to a pregnant woman or can affect reproduction capacity. This drug should be given to a pregnant woman only if clearly needed.
3.4 Drug Interactions: None known
3.5 Drug / Laboratory Test Interaction: None known
3.6 Carcinogenesis, mutagenesis, impairment of fertility: Not applicable

4. Use in Specifc Populations
4.1 Pediatric Use: Colocynthis-Homaccord® Injection Solution can be safely administered to children as young as 2 years. (see Dosage and Administration)
4.2 Nursing Mothers: It is not known whether any of the ingredients in Colocynthis-Homaccord® Injection Solution are excreted in human milk. However, because many drugs are excreted in human milk, Colocynthis-Homaccord® Injection Solution should be administered with caution to nursing mothers.
4.3 Geriatric use: Colocynthis-Homaccord® Injection Solution is safe to use in adults 12 years and older. (see Dosage and Administration)

5. Clinical Pharmacology
5.1 The exact mechanism of action of Colocynthis-Homaccord® Injection Solution is not fully understood.

6. Drug Abuse and Dependence
6.1 Not applicable for homeopathic drugs

7. Overdosage
7.1 Due to the low concentration of active ingredients in homeopathic preparations such as Colocynthis-Homaccord® Injection Solution, adverse reactions following over dosage are extremely unlikely. However, care must be taken not to exceed the recommended dosage.

8. How Supplied
8.1 Colocynthis-Homaccord® Injection Solution 1.1ml ampules: Packs of 10 ampules: NDC 50114-7065-1

9. Storage Conditions
9.1 Avoid freezing and excessive heat. Store at room temperature. Protect from light.

PACKAGE LABEL

ColocynthisHoma_Inj_Box.jpg
ColocynthisHoma_Inj insert_Rx2.jpg

ColocynthisHoma_Inj insert_Rx.jpg